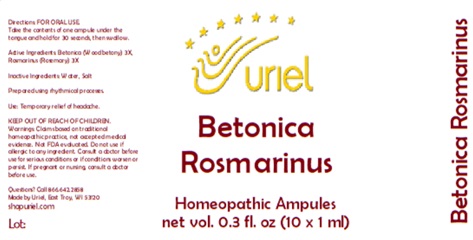 DRUG LABEL: Betonica Rosmarinus
NDC: 48951-2062 | Form: LIQUID
Manufacturer: Uriel Pharmacy Inc.
Category: homeopathic | Type: HUMAN OTC DRUG LABEL
Date: 20250122

ACTIVE INGREDIENTS: STACHYS OFFICINALIS 3 [hp_X]/1 mL; ROSMARINUS OFFICINALIS FLOWERING TOP 3 [hp_X]/1 mL
INACTIVE INGREDIENTS: WATER; SODIUM CHLORIDE

Betonica Rosmarinus

INDICATIONS AND USAGE

Directions: FOR ORAL USE.

DOSAGE AND ADMINISTRATION

Take the contents of one ampule under the tongue and hold for 30 seconds, then swallow.

ACTIVE INGREDIENT

Active Ingredients: Betonica (Wood betony) 3X, Rosmarinus (Rosemary) 3X

Inactive Ingredients: Water, Salt

Prepared using rhythmical processes.

PURPOSE

Use: Temporary relief of headache.

KEEP OUT OF REACH OF CHILDREN.

WARNINGS

Warnings: Claims based on traditional homeopathic practice, not accepted medical evidence. Not FDA evaluated. Do not use if allergic to any ingredient. Consult a doctor before use for serious conditions or if conditions worsen or persist. If pregnant or nursing, consult a doctor before use.

Questions? Call 866.642.2858

Made by Uriel, East Troy, WI 53120

shopuriel.com

Lot: